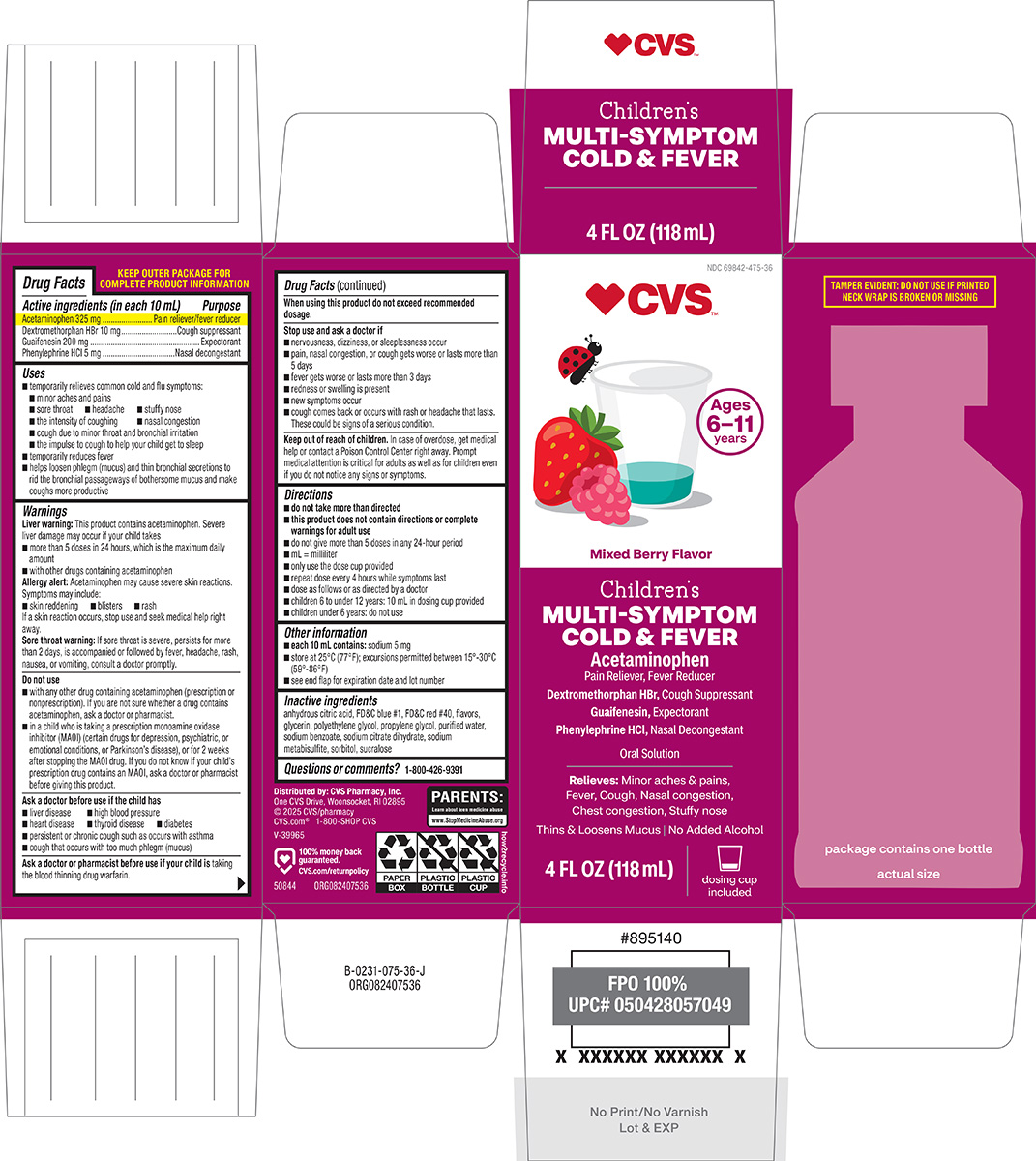 DRUG LABEL: Multi-Symptom Cold and Fever
NDC: 69842-475 | Form: SOLUTION
Manufacturer: CVS PHARMACY
Category: otc | Type: HUMAN OTC DRUG LABEL
Date: 20260225

ACTIVE INGREDIENTS: ACETAMINOPHEN 325 mg/10 mL; DEXTROMETHORPHAN HYDROBROMIDE 10 mg/10 mL; GUAIFENESIN 200 mg/10 mL; PHENYLEPHRINE HYDROCHLORIDE 5 mg/10 mL
INACTIVE INGREDIENTS: ANHYDROUS CITRIC ACID; FD&C BLUE NO. 1; FD&C RED NO. 40; GLYCERIN; POLYETHYLENE GLYCOL, UNSPECIFIED; PROPYLENE GLYCOL; WATER; SODIUM BENZOATE; TRISODIUM CITRATE DIHYDRATE; SODIUM METABISULFITE; SORBITOL; SUCRALOSE

CVS 44-075

Active ingredients (in each 10 mL)

Acetaminophen 325 mg
Dextromethorphan HBr 10 mg
Guaifenesin 200 mg
Phenylephrine HCl 5 mg

Purpose

Pain reliever/fever reducer
Cough suppressant
Expectorant
Nasal decongestant

Uses

- temporarily relieves common cold and flu symptoms:
  - minor aches and pains
  - sore throat
  - headache
  - stuffy nose
  - the intensity of coughing
  - nasal congestion
  - cough due to minor throat and bronchial irritation
  - the impulse to cough to help your child get to sleep
- temporarily reduces fever
- helps loosen phlegm (mucus) and thin bronchial secretions to rid the bronchial passageways of bothersome mucus and make coughs more productive

Warnings

Liver warning: This product contains acetaminophen. Severe liver damage may occur if your child takes

- more than 5 doses in 24 hours, which is the maximum daily amount
- with other drugs containing acetaminophen

Allergy alert: Acetaminophen may cause severe skin reactions. Symptoms may include:

- skin reddening
- blisters
- rash

If a skin reaction occurs, stop use and seek medical help right away.

Sore throat warning: If sore throat is severe, persists for more than 2 days, is accompanied or followed by fever, headache, rash, nausea, or vomiting, consult a doctor promptly.

Do not use

- with any other drug containing acetaminophen (prescription or nonprescription). If you are not sure whether a drug contains acetaminophen, ask a doctor or pharmacist.
- in a child who is taking a prescription monoamine oxidase inhibitor (MAOI) (certain drugs for depression, psychiatric, or emotional conditions, or Parkinson’s disease), or for 2 weeks after stopping the MAOI drug. If you do not know if your child’s prescription drug contains an MAOI, ask a doctor or pharmacist before giving this product.

Ask a doctor before use if the child has

- liver disease
- high blood pressure
- heart disease
- thyroid disease
- diabetes
- persistent or chronic cough such as occurs with asthma
- cough that occurs with too much phlegm (mucus)

Ask a doctor or pharmacist before use if your child is

taking the blood thinning drug warfarin.

When using this product

do not exceed recommended dosage.

Stop use and ask a doctor if

- nervousness, dizziness, or sleeplessness occur
- pain, nasal congestion, or cough gets worse or lasts more than 5 days
- fever gets worse or lasts more than 3 days
- redness or swelling is present
- new symptoms occur
- cough comes back or occurs with rash or headache that lasts. These could be signs of a serious condition.

Keep out of reach of children.

In case of overdose, get medical help or contact a Poison Control Center right away. Prompt medical attention is critical for adults as well as for children even if you do not notice any signs or symptoms.

Directions

- do not take more than directed
- this product does not contain directions or complete warnings for adult use
- do not give more than 5 doses in any 24-hour period
- mL = milliliter
- only use the dose cup provided
- repeat dose every 4 hours while symptoms last
- dose as follows or as directed by a doctor
- children 6 to under 12 years: 10 mL in dosing cup provided
- children under 6 years: do not use

Other information

- each 10 mL contains: sodium 5 mg
- store at 25°C (77°F); excursions permitted between 15°-30°C (59°-86°F)
- see end flap for expiration date and lot number

Inactive ingredients

anhydrous citric acid, FD&C blue #1, FD&C red #40, flavors, glycerin, polyethylene glycol, propylene glycol, purified water, sodium benzoate, sodium citrate dihydrate, sodium metabisulfite, sorbitol, sucralose

Questions or comments?

1-800-426-9391

Principal display panel

♥︎CVS™

NDC 69842-475-36

Ages
6–11
years

Mixed Berry Flavor

Children’s
MULTI-SYMPTOM
COLD & FEVER

Acetaminophen
Pain Reliever, Fever Reducer
Dextromethorphan HBr, Cough Suppressant
Guaifenesin, Expectorant
Phenylephrine HCl, Nasal Decongestant

Oral Solution

Relieves: Minor aches & pains,
Fever, Cough, Nasal congestion,
Chest congestion, Stuffy nose

Thins & Loosens Mucus | No Added Alcohol

4 FL OZ (118 mL)

dosing cup
included

TAMPER EVIDENT: DO NOT USE IF PRINTED
NECK WRAP IS BROKEN OR MISSING

Distributed by: CVS Pharmacy, Inc.
One CVS Drive, Woonsocket, RI 02895
© 2025 CVS/pharmacy
CVS.com® 1-800-SHOP CVS
V-39965

♥︎ 100% money back
guaranteed.
CVS.com/returnpolicy

50844 ORG082407536

package contains one bottle
actual size

PARENTS:
Learn about teen medicine abuse
www.StopMedicineAbuse.org

CVS 44-075